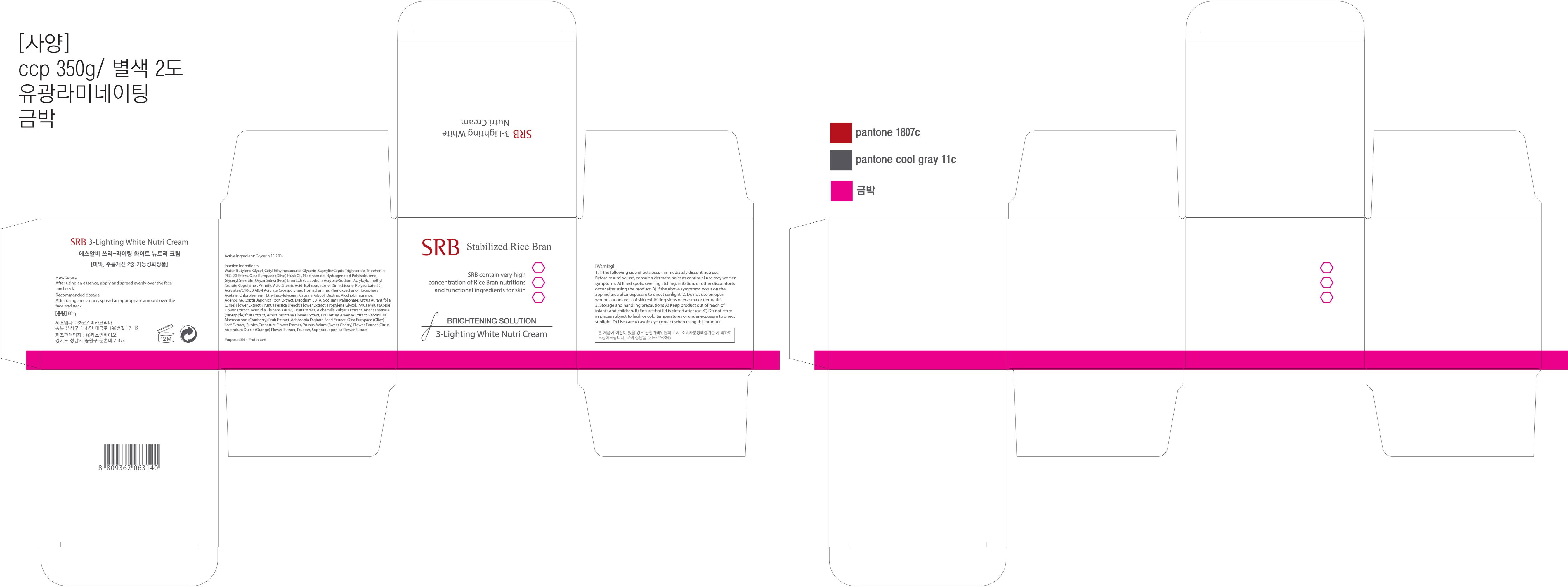 DRUG LABEL: SRB 3 Lighting White Nutri
NDC: 70218-010 | Form: CREAM
Manufacturer: CASINBIO CO., LTD.
Category: otc | Type: HUMAN OTC DRUG LABEL
Date: 20151112

ACTIVE INGREDIENTS: Glycerin 5.6 g/50 g
INACTIVE INGREDIENTS: Water; Butylene Glycol

ACTIVE INGREDIENT

Active Ingredient: Glycerin 11.20%

INACTIVE INGREDIENT

Inactive Ingredients: Water, Butylene Glycol, Cetyl Ethylhexanoate, Caprylic/Capric Triglyceride, Tribehenin PEG-20 Esters, Olea Europaea (Olive) Husk Oil, Niacinamide, Hydrogenated Polyisobutene, Glyceryl Stearate, Oryza Sativa (Rice) Bran Extract, Sodium Acrylate/Sodium Acryloyldimethyl Taurate Copolymer, Palmitic Acid, Stearic Acid, Isohexadecane, Dimethicone, Polysorbate 80, Acrylates/C10-30 Alkyl Acrylate Crosspolymer, Tromethamine, Phenoxyethanol, Tocopheryl Acetate, Chlorphenesin, Ethylhexylglycerin, Caprylyl Glycol, Dextrin, Alcohol, Fragrance, Adenosine, Coptis Japonica Root Extract, Disodium EDTA, Sodium Hyaluronate, Citrus Aurantifolia (Lime) Flower Extract, Prunus Persica (Peach) Flower Extract, Propylene Glycol, Pyrus Malus (Apple) Flower Extract, Actinidia Chinensis (Kiwi) Fruit Extract, Alchemilla Vulgaris Extract, Ananas sativus (pineapple) fruit Extract, Arnica Montana Flower Extract, Equisetum Arvense Extract, Vaccinium Macrocarpon (Cranberry) Fruit Extract, Adansonia Digitata Seed Extract, Olea Europaea (Olive) Leaf Extract, Punica Granatum Flower Extract, Prunus Avium (Sweet Cherry) Flower Extract, Citrus Aurantium Dulcis (Orange) Flower Extract, Fructan, Sophora Japonica Flower Extract

PURPOSE

Purpose: Skin Protectant

WARNINGS

Warnings: 1. If the following side effects occur, immediately discontinue use. Before resuming use, consult a dermatologist as continual use may worsen symptoms. A) If red spots, swelling, itching, irritation, or other discomforts occur after using the product. B) If the above symptoms occur on the applied area after exposure to direct sunlight. 2. Do not use on open wounds or on areas of skin exhibiting signs of eczema or dermatitis. 3. Storage and handling precautions A) Keep product out of reach of infants and children. B) Ensure that lid is closed after use. C) Do not store in places subject to high or cold temperatures or under exposure to direct sunlight. D) Use care to avoid eye contact when using this product.

KEEP OUT OF REACH OF CHILDREN

Keep product out of reach of infants and children.

How to use: After using an essence, apply and spread evenly over the face and neck

Recommended dosage

Recommended dosage: After using an essence, spread an appropriate amount over the face and neck